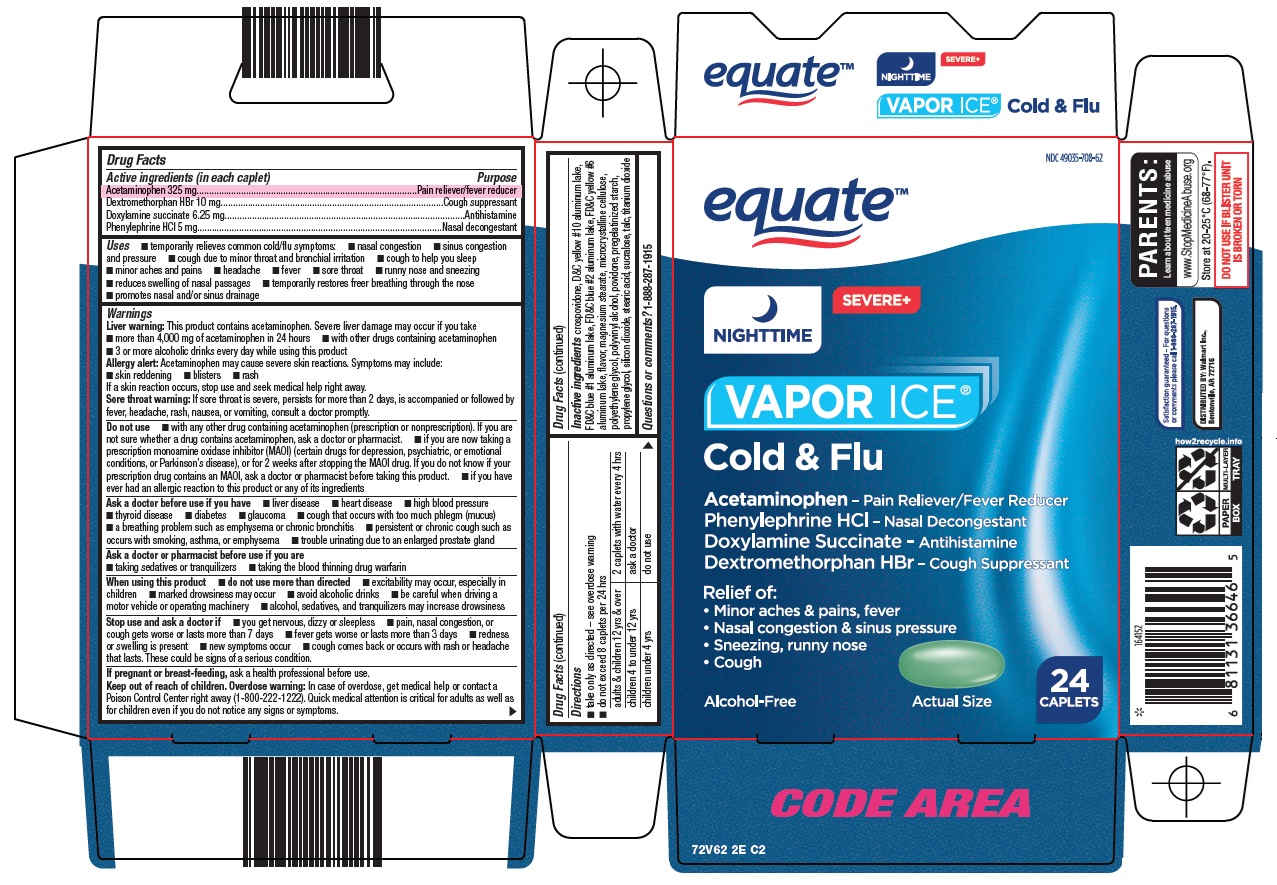 DRUG LABEL: equate vapor ice cold and flu
NDC: 49035-708 | Form: TABLET, FILM COATED
Manufacturer: Wal-Mart Stores Inc
Category: otc | Type: HUMAN OTC DRUG LABEL
Date: 20251114

ACTIVE INGREDIENTS: ACETAMINOPHEN 325 mg/1 1; DEXTROMETHORPHAN HYDROBROMIDE 10 mg/1 1; DOXYLAMINE SUCCINATE 6.25 mg/1 1; PHENYLEPHRINE HYDROCHLORIDE 5 mg/1 1
INACTIVE INGREDIENTS: CROSPOVIDONE (120 .MU.M); D&C YELLOW NO. 10; FD&C BLUE NO. 1; FD&C BLUE NO. 2; FD&C YELLOW NO. 6; MAGNESIUM STEARATE; MICROCRYSTALLINE CELLULOSE; POLYETHYLENE GLYCOL, UNSPECIFIED; POLYVINYL ALCOHOL, UNSPECIFIED; POVIDONE, UNSPECIFIED; PROPYLENE GLYCOL; SILICON DIOXIDE; STEARIC ACID; SUCRALOSE; TALC; TITANIUM DIOXIDE

Wal-Mart Vapor Ice® Cold & Flu Drug Facts

Active ingredients (in each caplet)

Acetaminophen 325 mg

Dextromethorphan HBr 10 mg

Doxylamine succinate 6.25 mg

Phenylephrine HCl 5 mg

Purpose

Pain reliever/fever reducer

Cough suppressant

Antihistamine

Nasal decongestant

Uses

- temporarily relieves common cold/flu symptoms:
- nasal congestion
- sinus congestion and pressure
- cough due to minor throat and bronchial irritation
- cough to help you sleep
- minor aches and pains
- headache
- fever
- sore throat
- runny nose and sneezing
- reduces swelling of nasal passages
- temporarily restores freer breathing through the nose
- promotes nasal and/or sinus drainage

Warnings

Liver warning: This product contains acetaminophen. Severe liver damage may occur if you take

- more than 4,000 mg of acetaminophen in 24 hours
- with other drugs containing acetaminophen
- 3 or more alcoholic drinks every day while using this product

Allergy alert: Acetaminophen may cause severe skin reactions. Symptoms may include:

- skin reddening
- blisters
- rash

If a skin reaction occurs, stop use and seek medical help right away.

Sore throat warning: If sore throat is severe, persists for more than 2 days, is accompanied or followed by fever, headache, rash, nausea, or vomiting, consult a doctor promptly.

Do not use

- with any other drug containing acetaminophen (prescription or nonprescription). If you are not sure whether a drug contains acetaminophen, ask a doctor or pharmacist.
- if you are now taking a prescription monoamine oxidase inhibitor (MAOI) (certain drugs for depression, psychiatric, or emotional conditions, or Parkinson’s disease), or for 2 weeks after stopping the MAOI drug. If you do not know if your prescription drug contains an MAOI, ask a doctor or pharmacist before taking this product.
- if you have ever had an allergic reaction to this product or any of its ingredients

Ask a doctor before use if you have

- liver disease
- heart disease
- high blood pressure
- thyroid disease
- diabetes
- glaucoma
- cough that occurs with too much phlegm (mucus)
- a breathing problem such as emphysema or chronic bronchitis
- persistent or chronic cough such as occurs with smoking, asthma, or emphysema
- trouble urinating due to an enlarged prostate gland

Ask a doctor or pharmacist before use if you are

- taking sedatives or tranquilizers
- taking the blood thinning drug warfarin

When using this product

- do not use more than directed
- excitability may occur, especially in children
- marked drowsiness may occur
- avoid alcoholic drinks
- be careful when driving a motor vehicle or operating machinery
- alcohol, sedatives, and tranquilizers may increase drowsiness

Stop use and ask a doctor if

- you get nervous, dizzy or sleepless
- pain, nasal congestion, or cough gets worse or lasts more than 7 days
- fever gets worse or lasts more than 3 days
- redness or swelling is present
- new symptoms occur
- cough comes back or occurs with rash or headache that lasts. These could be signs of a serious condition.

If pregnant or breast-feeding,

ask a health professional before use.

Directions

- take only as directed – see overdose warning
- do not exceed 8 caplets per 24 hrs

adults & children 12 yrs & over | 2 caplets with water every 4 hrs
children 4 to under 12 yrs | ask a doctor
children under 4 yrs | do not use

Inactive ingredients

crospovidone, D&C yellow #10 aluminum lake, FD&C blue #1 aluminum lake, FD&C blue #2 aluminum lake, FD&C yellow #6 aluminum lake, flavor, magnesium stearate, microcrystalline cellulose, polyethylene glycol, polyvinyl alcohol, povidone, pregelatinized starch, propylene glycol, silicon dioxide, stearic acid, sucralose, talc, titanium dioxide

Questions or comments?

1-888-287-1915

Package/Label Principal Display Panel

equate™

NIGHTTIME

SEVERE+

VAPOR ICE® Cold & Flu

Acetaminophen – Pain Reliever/Fever Reducer

Phenylephrine HCl – Nasal Decongestant

Doxylamine Succinate – Antihistamine

Dextromethorphan HBr – Cough Suppressant

Relief of:

• Minor aches & pains, fever

• Nasal congestion & sinus pressure

• Sneezing, runny nose

• Cough

Alcohol-Free

Actual Size

24 CAPLETS